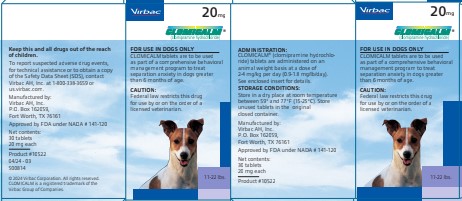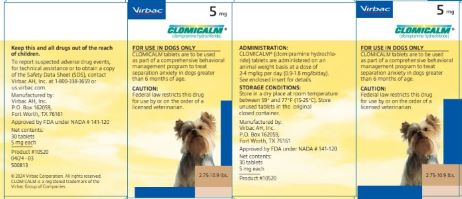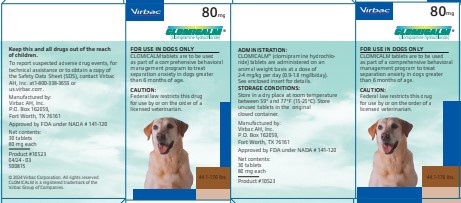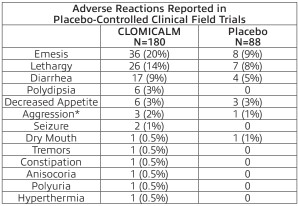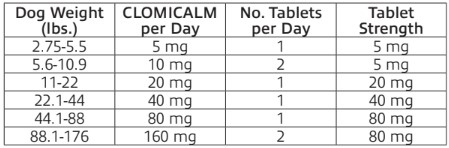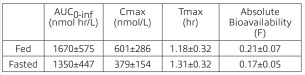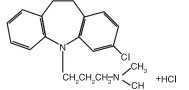 DRUG LABEL: CLOMICALM
NDC: 51311-140 | Form: TABLET
Manufacturer: Virbac AH, Inc.
Category: animal | Type: PRESCRIPTION ANIMAL DRUG LABEL
Date: 20240729

ACTIVE INGREDIENTS: CLOMIPRAMINE HYDROCHLORIDE 5 mg/1 1

CLOMICALM® (clomipramine hydrochloride)

Caution

Federal law restricts this drug to use by or on the order of a licensed veterinarian.

Description

CLOMICALM® (clomipramine hydrochloride) tablets belong to the dibenzazepine class of tricyclic antidepressants. Clomipramine hydrochloride is 3-chloro-5[3-(dimethyl-amino)propyl]-10,11dihydro-5H dibenz[b,f]azepine monohydrochloride. CLOMICALM tablets are oblong, light brown in color and contain clomipramine hydrochloride formulated together with meat components. The molecular weight of clomipramine hydrochloride is 351.3. The structural formula is:

Clinical Pharmacology

Clomipramine hydrochloride reduces the clinical signs of separation anxiety by affecting serotonergic and noradrenergic neuronal transmission in the central nervous system. While clomipramine hydrochloride can cause lethargy in dogs (see Adverse Reactions) its mode of action is not as a sedative. Clomipramine hydrochloride’s capacity to inhibit re-uptake of serotonin in the central nervous system is believed to be the primary mechanism of action. Clomipramine hydrochloride is rapidly absorbed when administered orally. A single-dose crossover study involving 12 dogs evaluated clomipramine hydrochloride bioavailability after IV (2 mg/kg) and oral (4 mg/kg) administration in either a fed or fasted state. The
administration of clomipramine hydrochloride in the presence of food resulted in an increase in the rate and extent of drug absorption as shown in the following table (mean ±SD):

The absolute bioavailability is approximately 25% greater in fed dogs. The apparent terminal plasma half-life ranges from approximately 2 to 9 hours in fed and 3 to 21 hours in fasted dogs. The difference and variability in apparent half-life estimates may be attributable to prolonged drug absorption in the fasted state. The relatively large volume of distribution (3.8±0.8 L/kg) suggests that the drug is widely distributed throughout the body. Clomipramine is primarily metabolized in the liver.

Indications and Usage: CLOMICALM tablets are to be used as part of a comprehensive behavioral management program to treat separation anxiety in dogs greater than 6 months of age. Inappropriate barking or destructive behavior, as well as inappropriate elimination (urination or defecation) may be alleviated by the use of CLOMICALM tablets in conjunction with behavior modification.

Separation anxiety is a complex behavior disorder displayed when the owner (or other attachment figure) leaves the dog. The signs of
separation anxiety evaluated in controlled trials were vocalization, destructive behavior, excessive salivation, and inappropriate elimination. In the absence of the owner or attachment figure, dogs with separation anxiety may exhibit one or more of these clinical signs. Although the owner (attachment figure) may inadvertently misinterpret this behavior, which only happens in their absence, as spiteful, it is thought to be the result of anxiety experienced by the dog. Punishment is not considered appropriate for a dog with separation anxiety.

Proper recognition of clinical signs, including a complete patient history and assessment of the patient’s household environment, is essential to accurately diagnose and treat separation anxiety. The use of CLOMICALM tablets should not replace appropriate behavioral and environmental management but should be used to facilitate a comprehensive behavior management program.

Contraindications

CLOMICALM tablets are contraindicated in dogs with known hypersensitivity to clomipramine or other tricyclic antidepressants.

CLOMICALM tablets should not be used in male breeding dogs. Testicular hypoplasia was seen in dogs treated for 1 year at 12.5 times the maximum daily dose.

CLOMICALM tablets should not be given in combination, or within 14 days before or after treatment with a monoamine oxidase inhibitor [e.g., selegiline hydrochloride (L-deprenyl), amitraz].

CLOMICALM tablets are contraindicated for use in dogs with a history of seizures or concomitantly with drugs which lower the seizure threshold.

Human Warnings

Not for use in humans. Keep out of reach of children. In case of accidental ingestion seek medical attention immediately. In
children, accidental ingestion should be regarded as serious. There is no specific antidote for clomipramine. Overdose in humans causes anticholinergic effects including effects on the central nervous (e.g., convulsions) and cardiovascular (e.g., arrhythmia, tachycardia) systems. People with known hypersensitivity to clomipramine should administer the product with caution.

Precautions

General: CLOMICALM tablets are not recommended for other behavior problems, such as aggression (see Adverse Reactions). Studies to establish the safety and efficacy of CLOMICALM tablets in dogs less than 6 months of age have not been conducted.

Diagnosis: It is critical to conduct a comprehensive physical examination, including appropriate laboratory tests, and to obtain a thorough history and assessment of the patient’s household environment, to rule-out causes of inappropriate behavior unrelated to separation anxiety before prescribing CLOMICALM tablets. Periodic reassessment of hematological and serum biochemical data during the administration of this medication is advised. Veterinarians should be familiar with the risks and benefits of the treatment of behavioral disorders in dogs before initiating therapy. Inappropriate use of CLOMICALM tablets, i.e., in the absence of a diagnosis or without concurrent behavioral modification, may
expose the animal to unnecessary adverse effects and may not provide any lasting benefit of therapy.

Drug Interactions: Recommendations on the interaction between clomipramine and other medications are extrapolated from data generated in humans. Plasma levels of tricyclic antidepressants have been reported to be decreased by the concomitant administration of hepatic enzyme inducers (e.g., barbiturates, phenytoin); therefore plasma concentrations of clomipramine may be decreased by the concomitant administration of
phenobarbital. Plasma levels of closely related tricyclic antidepressants have been reported to be increased by the concomitant administration of hepatic enzyme inhibitors (e.g., cimetidine, fluoxetine). Tricyclic antidepressants themselves may exhibit hepatic enzyme inhibition and possibly increase plasma levels of barbiturates (phenobarbital). Caution is advised in using clomipramine with anticholinergic or sympathomimetic drugs or with other CNS-active drugs, including general anesthetics and neuroleptics. Prior to elective surgery with general anesthetics, clomipramine
should be discontinued for as long as clinically feasible.

Use in Concomitant Illness: Use with caution in dogs with cardiovascular disease. At 20 mg/kg/day (5X the maximum recommended dose), bradycardia and arrhythmias (atrioventricular node block and ventricular extrasystole) were observed in dogs. Because of its anticholinergic properties, clomipramine should be used with caution in patients with increased intraocular pressure, a history of narrow angle glaucoma, urinary retention or reduced gastrointestinal motility. Because clomipramine is principally metabolized in the liver, caution is advised in using this medication in the presence of preexisting liver disease.

Reproductive Safety: Safety studies to determine the effects of CLOMICALM tablets in pregnant or lactating female dogs have not been conducted. CLOMICALM tablets should not be used in breeding males (See Contraindications).

Efficacy

Dose Establishment: A 12 week, placebo-controlled, multi-site clinical trial was conducted in the US and Europe to establish an effective dose of CLOMICALM tablets in dogs. Treatment with CLOMICALM tablets, at 2 - 4 mg/kg/day divided twice daily, in conjunction with behavioral
modification (desensitization and counterconditioning) was more effective than behavior modification alone in reducing the signs of separation anxiety in dogs.

Dose Confirmation: In another placebo-controlled, multi-site clinical trial, CLOMICALM tablets at 2 - 4 mg/kg/day given either once daily or divided twice daily showed significant improvement in resolving signs of separation anxiety when tested against behavioral modification alone (desensitization and counterconditioning). In this 8 week study, the rate of improvement of the dogs receiving CLOMICALM tablets with behavioral modification was significantly faster than the rate of improvement of the dogs receiving behavioral modification alone. After one week on trial, 47% of the dogs receiving CLOMICALM tablets once or twice (divided dose) daily in conjunction with behavioral modification showed clinical improvement compared to improvement in 29% of the dogs receiving behavioral modification alone.

Safety

CLOMICALM® (clomipramine hydrochloride) tablets were demonstrated to be well-tolerated in dogs at the recommended label dose of 2-4 mg/
kg/day. In a six month target animal safety study, beagle dogs were dosed daily at 4 (1X), 12 (3X), and 20 (5X) mg/kg/day. Emesis was seen
in all groups including the dogs receiving placebo, but occurred more frequently in dogs receiving 12 and 20 mg/kg. Decreased activity was
also seen in dogs receiving the 12 and 20 mg/kg. There were no apparent treatment-related alterations in the following: body weights, physical
examination findings, electrocardiograph examinations, hematology or biochemistry parameters, ophthalmoscopic examinations, macroscopic
or microscopic organ examinations and organ weights. Average food and water consumption over the 26 week period was similar for control
and treated groups. In a one year study, pure bred dogs were dosed daily at 12.5 (3X), 50 (12.5X), and 100 (25X) mg/kg/day. Emesis and mydriasis were observed within 15 minutes to one hour after dosing in dogs receiving 12.5, 50, and 100 mg/kg/day and lethargy was observed within 1 hour of dosing in dogs receiving 50 and 100 mg/kg. Testicular hypoplasia was seen in dogs receiving 50 mg/kg. At 100 mg/kg/day (25X)
convulsions and eventual death occurred in five out of the eight dogs.

Adverse Reactions

Frequency and category of adverse reactions observed in dogs dosed with CLOMICALM tablets or placebo were observed in multisite clinical studies as follows.

*These dogs displayed growling behavior towards either humans or other dogs.

Post-Approval Experience: Although not all adverse reactions are reported, the following adverse reactions are based on voluntary post-approval adverse drug experience reporting: lethargy/depression, anorexia, elevation in liver enzymes, vomiting and diarrhea. Hepatobiliary disease has occurred, especially in the presence of pre-existing conditions or with concurrent administration of drugs metabolized via the hepatic system. Additionally, in an overdose situation, the following signs have been reported: ataxia, convulsion(s), anticholinergic effects (e.g., mydriasis, bradycardia, tachycardia, and arrhythmia) and vocalization. To report suspected adverse drug events, for technical assistance or to
obtain a copy of the Safety Data Sheet (SDS), contact Virbac AH, Inc. at 1-800-338-3659 or us.virbac.com. For additional information about
adverse drug experience reporting for animal drugs, contact FDA at 1-888-FDA-VETS or http://www.fda.gov/reportanimalae.

Dosage and Administration

The recommended daily dose of CLOMICALM tablets is 2 to 4 mg/kg/day (0.9 -1.8 mg/lb/day) (see dosing table below). It can be administered as a single daily dose or divided twice daily based on patient response and/or tolerance of the side effects. It may be prudent to initiate treatment in divided doses to minimize side effects by permitting tolerance to side effects to develop or allowing the patient time to adapt if tolerance does not develop. To reduce the incidence of vomiting that may be experienced by some dogs, CLOMICALM tablets may be given with a small amount of food.

The specific methods of behavioral modification used in clinical trials involved desensitization and counterconditioning techniques. Since the manifestation of separation anxiety can vary according to the individual dog, it is advised that a specific behavior modification plan be developed based on a professional assessment of each individual case.

Once the desired clinical effect is achieved and the owners have successfully instituted the appropriate behavioral modification, the dose of CLOMICALM tablets may be reduced to maintain the desired effect or discontinued. Withdrawal side effects were not reported in studies with CLOMICALM tablets in dogs. However, in clinical practice, it is recommended to taper the individual patient dose while continuing to monitor the dog’s behavior and clinical status through the dose reduction or withdrawal period. Continued behavioral modification is recommended to prevent recurrence of the clinical signs.

The effectiveness and clinical safety of CLOMICALM tablets for long-term use (i.e., for more than 12 weeks) has not been evaluated.

Professional judgment should be used in monitoring the patient’s clinical status, response to therapy and tolerance to side effects to determine the need to continue treatment with CLOMICALM tablets and to continue to rule-out physiological disorders which may complicate the diagnosis and treatment of separation anxiety.

Storage Conditions

Store in a dry place at controlled room temperature, between 59° and 77°F (15-25°C). Store unused tablets in the original closed container.

How Supplied

CLOMICALM tablets are available in 5, 20, 40 and 80 mg tablet strengths in color-coded packaging for oral administration to dogs.

Keep this and all drugs out of reach of children.

Manufactured by: Virbac AH, Inc.
P.O. Box 162059, Fort Worth, TX 76161, USA
Approved by FDA under NADA # 141-120
04/24 - 03
302304
© 2024 Virbac Corporation. All rights reserved. CLOMICALM is a
registered trademark of the Virbac Group of Companies.

Information for Dog Owners

Caution:
Federal law restricts this drug to use by or on the order of a licensed veterinarian.

Introduction:
Virbac AH, Inc. encourages you to take the time to read this package insert which describes the use of CLOMICALM tablets for the treatment of separation anxiety in conjunction with behavior modification (training) in dogs. CLOMICALM tablets do not act as a sedative. Instead, CLOMICALM tablets help to reduce the anxiety associated with this condition, thus allowing your dog to more effectively benefit from behavior
training. After reading this insert, if you have any questions about the use of CLOMICALM tablets, please consult your veterinarian.

Description:
CLOMICALM tablets belong to the dibenzazepine class of tricyclic antidepressants. Clomipramine hydro-chloride is 3-chloro-5[3-(dimethyl-amino)propyl]-10,11-dihydro-5H-dibenz[b,f]azepine monohydrochloride. CLOMICALM tablets are oblong, light brown in color and contain clomipramine-hydrochloride formulated together with meat components.

Indications and Usage:
CLOMICALM tablets are to be used as part of a comprehensive behavioral management program to treat separation anxiety in dogs greater than
6 months of age. Inappropriate barking or destructive behavior, as well as inappropriate elimination (urination or defecation) may be alleviated by the use of CLOMICALM tablets in conjunction with behavior modification. Separation anxiety is a complex behavior disorder displayed when the owner (or other attachment figure) leaves the dog. In the absence of the owner or attachment figure, dogs with separaton anxiety may exhibit one or more clinical signs. The signs of separation anxiety evaluated in controlled trials were vocalization, destructive behavior, excessive salivation, and inappropriate elimination. Although it may appear that this behavior, which only happens in the dog owner’s absence, is a spiteful action, this behavior is thought to be a result of anxiety experienced by the dog. Therefore, punishment would not be appropriate for the dog with this behavior.

Behavior Modification (Training)
Behavior training is a necessary component of therapy with CLOMICALM tablets. In clinical trials, specific behavior training techniques were used at the following times:
• when the owner interacted with the dog while at home
• when the owner was preparing to leave the home
• when the owner returned home and greeted the dog
Since the methods used for behavior training can vary according to patient needs, it is important that you follow the instructions provided by your veterinarian regarding the specific techniques recommended for modifying your dog’s behavior.

Contraindications:
CLOMICALM tablets are contraindicated in dogs with known hypersensitivity to clomipramine or related tricyclic antidepressants.

CLOMICALM tablets should not be used in male breeding dogs. Testicular hypoplasia was seen in dogs treated for 1 year at 12.5 times the maximum daily dose.

CLOMICALM tablets should not be given in combination, or within 14 days before or after treatment with a monoamine oxidase inhibitor [e.g. selegiline hydrochloride (L-deprenyl), amitraz].

CLOMICALM tablets are contraindicated for use in dogs with a history of seizures or concomitantly with drugs which lower the seizure threshold.

Human Warnings:
Not for use in humans. KEEP OUT OF REACH OF CHILDREN. In case of accidental ingestion seek medical attention immediately. In children, accidental ingestion should be regarded as serious. There is no specific antidote for clomipramine. Overdose in humans causes anticholinergic effects including effects on the central nervous (e.g., convulsions) and cardiovascular (e.g., arrhythmia, tachycardia) systems. People with known
hypersensitivity to clomipramine should administer the product with caution.

Precautions:
It is important that your dog be closely monitored by your veterinarian while on a treatment plan with CLOMICALM tablets and behavior training. You must inform your veterinarian of any current or future medications you are administering to your dog. The use of CLOMICALM tablets in
conjunction with certain other drugs or when your dog has other illnesses may be contraindicated or increase the risks of adverse reactions. It is important that you inform your veterinarian of any changes in your dog’s environment including, but not limited to, a new family member, a new pet, a move to a new location, or a change in your existing daily schedule. Some changes may result in an altered response to therapy.

It is important to inform your veterinarian of any perceived changes in your dog’s behavior, appetite, or overall health while administering any medication. Some dogs display a temporary lethargy with the first few days of CLOMICALM® (clomipramine hydrochloride) tablets treatment. In some cases, signs of separation anxiety, such as vocalization, may temporarily increase at the initiation of treatment. In an overdose situation, seek veterinary attention for your pet as soon as possible.

The safety and efficacy of CLOMICALM tablets have not been established in dogs less than 6 months of age or in pregnant or lactating female dogs. CLOMICALM tablets should not be used in breeding male dogs (see Contraindications). CLOMICALM tablets are not recommended for other behavior problems, such as aggression.

Efficacy:
CLOMICALM tablets were tested in clinical trials involving client-owned dogs to determine effectiveness. CLOMICALM tablets, at 2 – 4 mg/kg/day (0.9 – 1.8 mg/pound/day) when used in conjunction with behavior training, accelerated both the time to improvement and the final result of separation anxiety therapy compared to behavioral training alone.

Adverse Reactions:
The following adverse reactions have been reported associated with administration of CLOMICALM tablets: lethargy/depression, vomiting, diarrhea, elevation in liver enzymes, convulsion(s), increased heart rate, decreased heart rate, increased thirst and confusion. Liver disease has
occurred, especially in the presence of pre-existing conditions or with concurrent administration of drugs metabolized by the liver. In overdoses, signs such as vomiting, lethargy or depression, weakness and incoordination, dilated pupils, and vocalization may occur. Consult with your veterinarian if your dog experiences these or any other conditions.

To report suspected adverse drug events, for technical assistance or to obtain a copy of the Safety Data Sheet, contact Virbac AH, Inc. at 1-800-338-3659 or us.virbac.com. For additional information about adverse drug experience reporting for animal drugs, contact FDA at 1-888-FDA-VETS or http://www.fda.gov/reportanimalae.

Dosage and Administration:
The recommended daily dose of CLOMICALM tablets is 2 to 4 mg/kg/day (0.9 – 1.8 mg/lb/day) (see dosing table below). Your veterinarian will instruct you to give the drug either once a day or divide the daily dose into 2 separate doses depending on your dog’s response to the drug or tolerance to any side effects. CLOMICALM tablets may be given with a small amount of food in an attempt to reduce the incidence of vomiting that may be experienced by some dogs. If a dose is missed, the next dose should be administered (without doubling) at the next scheduled dosing time.

Your veterinarian may decrease the dose or discontinue treatment with CLOMICALM tablets depending on your dog’s response to treatment. Continued behavior training is recommended, even after cessation of drug therapy.

Storage Conditions:
Store in a dry place at controlled room temperature, between 59° and 77°F (15-25°C). Store unused tablets in the original closed container.

How Supplied:
CLOMICALM tablets are available in 5, 20, 40 and 80 mg tablet strengths in color-coded packaging for oral administration to dogs.

KEEP THIS AND ALL DRUGS OUT OF REACH OF CHILDREN.

Manufactured by: Virbac AH, Inc.
P.O. Box 162059 Fort Worth, TX 76161, USA
Approved by FDA under NADA # 141-120
04/24 - 03
302304
© 2024 Virbac Corporation. All rights reserved. CLOMICALM is a
registered trademark of the Virbac Group of Companies.